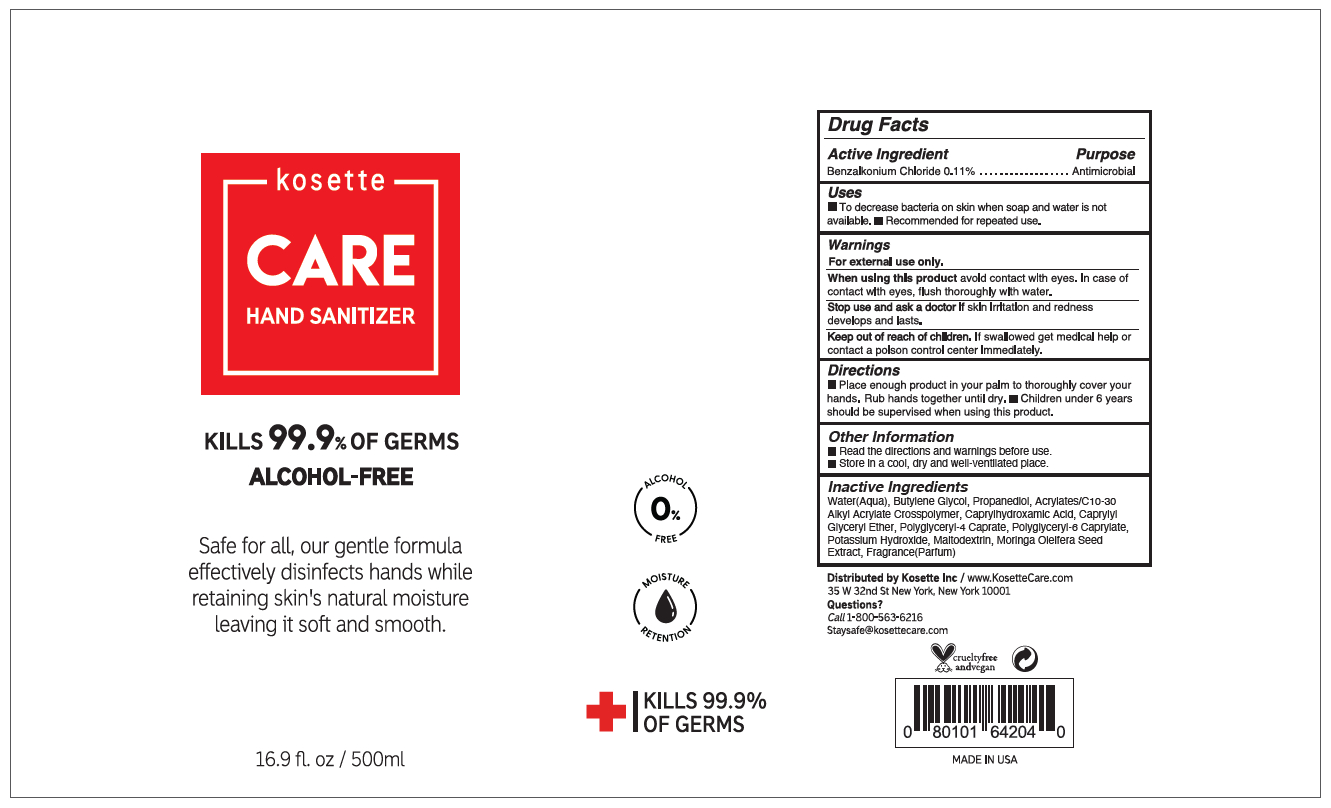 DRUG LABEL: Kosette CARE Hand Sanitizer Alcohol-Free
NDC: 73284-420 | Form: GEL
Manufacturer: Innovation Labs, Inc.
Category: otc | Type: HUMAN OTC DRUG LABEL
Date: 20200701

ACTIVE INGREDIENTS: BENZALKONIUM CHLORIDE 0.0011 mg/1 mL
INACTIVE INGREDIENTS: CAPRYLHYDROXAMIC ACID; MORINGA OLEIFERA SEED OIL; CAPRYLYL GLYCERYL ETHER; POLYGLYCERIN-6; BUTYLENE GLYCOL; WATER; PROPANEDIOL; CARBOMER INTERPOLYMER TYPE A (55000 CPS); POTASSIUM HYDROXIDE; POLYGLYCERYL-4 CAPRATE; MALTODEXTRIN

Kosette CARE Hand Sanitizer 500 mL

Active Ingredient

Benzalkonium Chloride 0.11%

Purpose

Antimicrobial

Uses

- To decrease bacteria on skin when soap and water is not available.
- Recommended for repeated use.

Warnings

- For external use only.

- When using this product avoid contact with eyes. In case of contact with eyes, flush thoroughly with water.

- Stop use and ask a doctor if skin irritation or redness develops and lasts.

- Keep out of reach of children. If swallowed, get medical help or contact a Poison Control Center right away.

Directions

- Place enough product in your palm to thoroughly cover your hands. Rub hands together until dry.
- Children under 6 years should be supervised when using this product.

Other information

- Read the directions and warnings before use.
- Store in a cool, dry and well-ventilated place.

Inactive ingredients

water(aqua), butylene glycol, propanediol, acrylates/c10-30 alkyl acrylate crosspolymer, caprylhydroxamic acid, caprylyl glyceryl ether, polyglyceryl-4 caprate, polyglyceryl-6 caprylate, potassium hydroxide, maltodextrin, moringa oleifera seed extract, frangrance(parfum)

Package Label - Principal Display Panel

Kosette

CARE

HAND SANITIZER

KILLS 99.9% OF GERMS

ALCOHOL-FREE

Safe for all, our gentle formula

effectively disinfects hands while

retaining skin's natural moisture

leaving it soft and smooth.

16.9 fl.oz / 500 ml